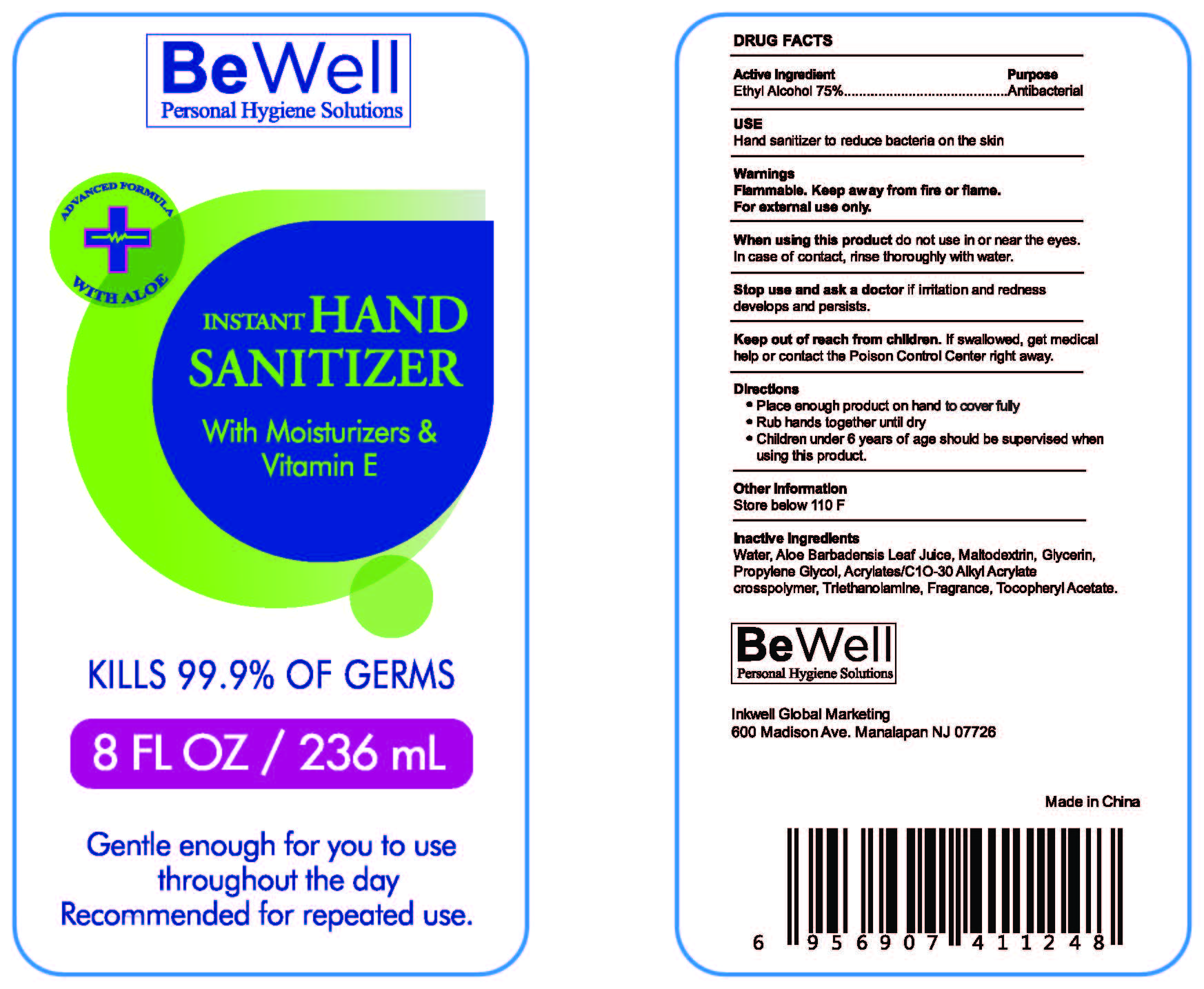 DRUG LABEL: Hand Sanitizer
NDC: 77512-008 | Form: GEL
Manufacturer: Inkwell Global Marketing Corp.
Category: otc | Type: HUMAN OTC DRUG LABEL
Date: 20200518

ACTIVE INGREDIENTS: ALCOHOL 75 mL/100 mL
INACTIVE INGREDIENTS: MALTODEXTRIN; PROPYLENE GLYCOL; WATER; ALOE VERA LEAF; GLYCERIN; CARBOMER INTERPOLYMER TYPE A (55000 CPS); TROLAMINE; .ALPHA.-TOCOPHEROL ACETATE

Active Ingredient
Ethyl Alcohol 75%

Purpose
Antibacterial

Uses

Hand sanitizer to reduce bacteria on the skin.

Warnings

Flammable. Keep away from fire or flame.

For external use only.

When using this product do not use in or near the eyes.In case of contact, rinse eyes thoroughly with

water.

Stop use and ask a doctor if irritation and redness develops and persists.

Keep out of reach of children. If swallowed, get medical help or contact the Poison Control Center right away.

Directions

- Place enough product on hand to cover fully
- Rub hands together until dry
- Children under 6 years of age should be supervised when using this product.

Other Information

Store below 110 F.

Inactive Ingredients

Water, Aloe Barbadensis Leaf Juice, Maltodextrin,Glycerin, Propylene Glycol, Acrylates/C1O-30 Alkyl Acrylate crosspolymer, Triethanoamine, Fragrance, Tocopheryl Acetate.